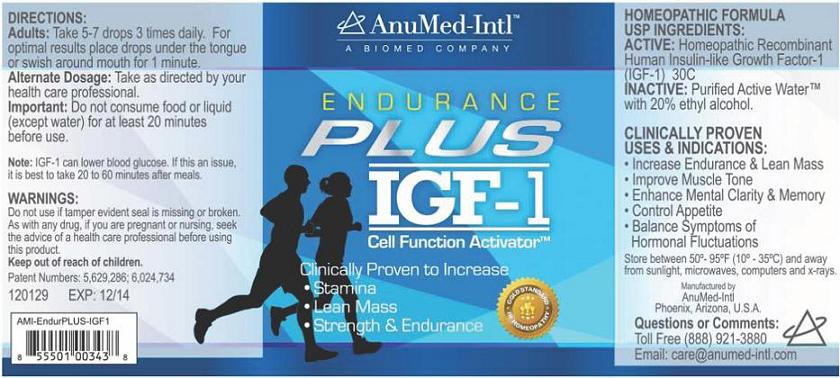 DRUG LABEL: IGF-1 Endurance Plus
NDC: 50970-003 | Form: LIQUID
Manufacturer: AnuMed International LLC
Category: homeopathic | Type: HUMAN OTC DRUG LABEL
Date: 20231129

ACTIVE INGREDIENTS: MECASERMIN 30 [hp_C]/30 mL
INACTIVE INGREDIENTS: ALCOHOL; WATER

ENDURANCE PLUS IGF-1
Cell Function ActivatorTM

ACTIVE INGREDIENTS:

Homeopathic Recombinant Human Insulin-like Growth Factor-1 (IGF-1) 30C

PURPOSE:

Increase Endurance & Lean Mass, Improve Muscle Tone, Enhance Mental Clarity & Memory, Control Appetite, Balance Symptoms of Hormonal Fluctuations

USES:

Increase Endurance & Lean Mass, Improve Muscle Tone, Enhance Mental Clarity & Memory, Control Appetite, Balance Symptoms of Hormonal Fluctuations

WARNINGS:

Do Not Use

if tamper evident seal is missing or broken.

Note: IGF-1 can lower blood glucose. If this is an issue, it is best to take 20 to 60 minutes after meals.

Pregnancy or Breast Feeding

As with any drug, it you are pregnant or nursing a baby, consult a health care professional before using this product.

DIRECTIONS:

Adults: Take 5-7 drops 3 times daily. For optimal results place drops under the tongue or swish around mouth for 1 minute.

Alternate Dosage: Take as directed by your health care professional.

Important: Do not consume food or liquid (except water) for at least 20 minutes before use.

INACTIVE INGREDIENTS:

Purified Active WaterTM, 20% ethyl alcohol.

QUESTIONS OR COMMENTS:

Toll Free: (888) 921-3880

Email: care@anumed-intl.com

Manufactured by:
Anumed International LLC™
Phoenix Arizona

Patent Numbers: 5,629,286; 6,024,734

PACKAGE/LABEL PRINCIPAL DISPLAY PANEL

AnuMed Intl™

A Biomed Company

ENDURANCE PLUS IGF-1

Cell Function ActivatorTM

Clinically Proven to Increase

- Stamina
- Lean Mass
- Strength & Endurance

Gold Standard in Homeopathy